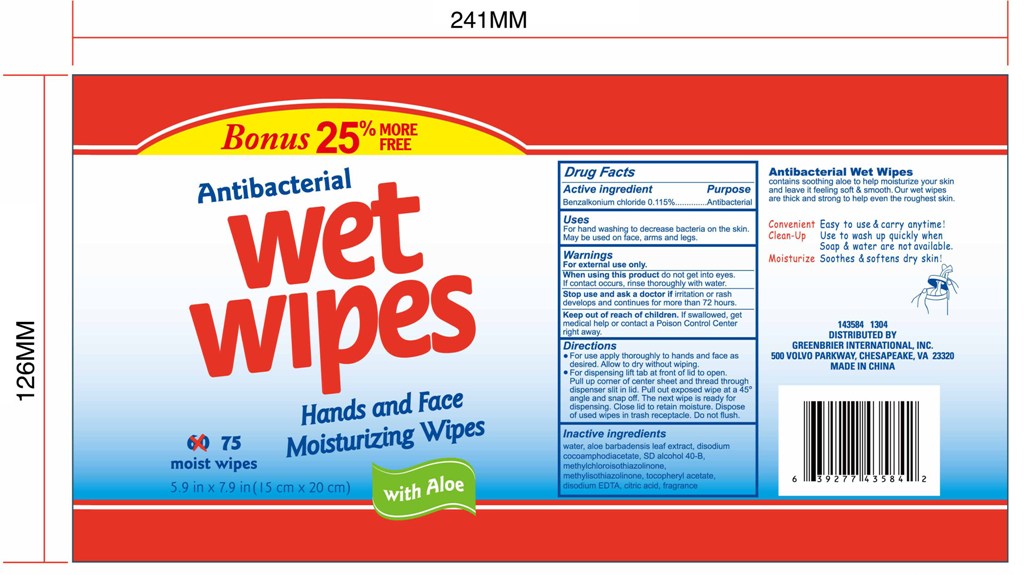 DRUG LABEL: Antibacterial Wet Wipes
NDC: 42255-900 | Form: SWAB
Manufacturer: ZHEJIANG GREENFACE HOUSEWARES CO., LTD.
Category: otc | Type: HUMAN OTC DRUG LABEL
Date: 20180108

ACTIVE INGREDIENTS: BENZALKONIUM CHLORIDE 0.115 g/100 g
INACTIVE INGREDIENTS: DISODIUM COCOAMPHODIACETATE; ALOE VERA LEAF; ALPHA-TOCOPHEROL ACETATE; CITRIC ACID ACETATE; EDETATE DISODIUM; METHYLCHLOROISOTHIAZOLINONE; WATER

ANTIBACTERIAL WET WIPES

Active ingredient

Benzalkonium chloride 0.115%

Purpose

Antibacterial

Uses

For hand washing to decrease bacteria on the skin.

May be used on face, arms and legs.

Warnings

For external use only.

When using this product do not get into eyes.

If contact occurs, rinse thoroughly with water.

Stop use and ask a doctor if irritation or rash

develops and continues for more than 72 hours.

Keep out of reach of children. If swallowed, get

medical help or contact a Poison Control Center

right away.

Keep out of reach of children

if swallowed

get medical help or contact a Poison Control Center right away.

Directions

For use apply thoroughly to hands and face as

desired. Allow to dry without wiping.

For dispensing lift tab at front of lid to open.

Pull up corner of center sheet and thread through

dispenser slit in lid. Pull out exposed wipe at a 45

angle and snap off. The next wipe is ready for

dispensing. Close lid to retain moisture. Dispose

of used wipes in trash receptacle. Do not flush.

INACTIVE INGREDIENT

Water
Aloe barbadensis leaf extract
Disodium cocoamphodiacetate
SD alcohol 40-B
Methylchloroisothiazolinone
Methylisothiazolinone
Tocopheryl acetate
Disodium EDTA
Citric acid